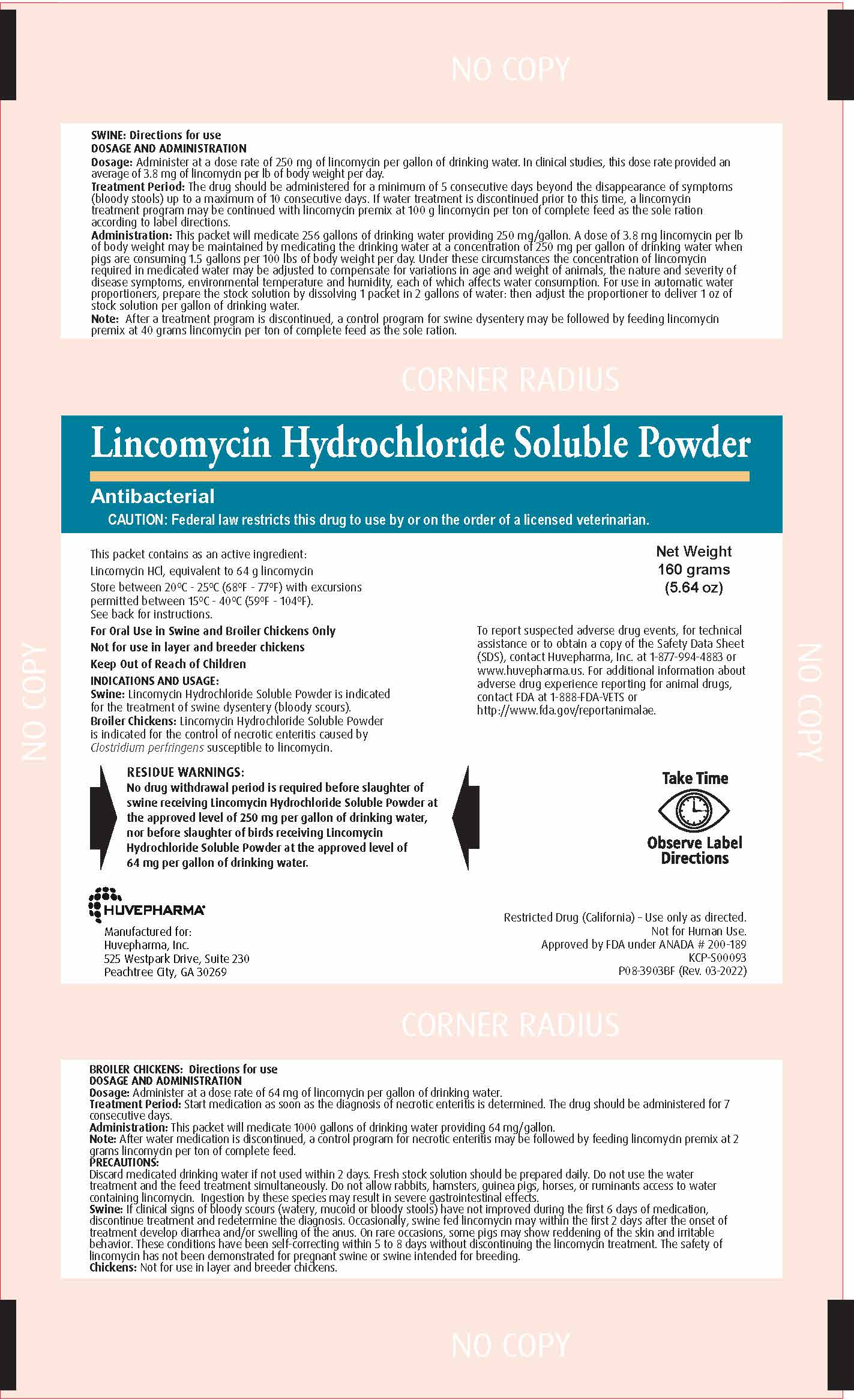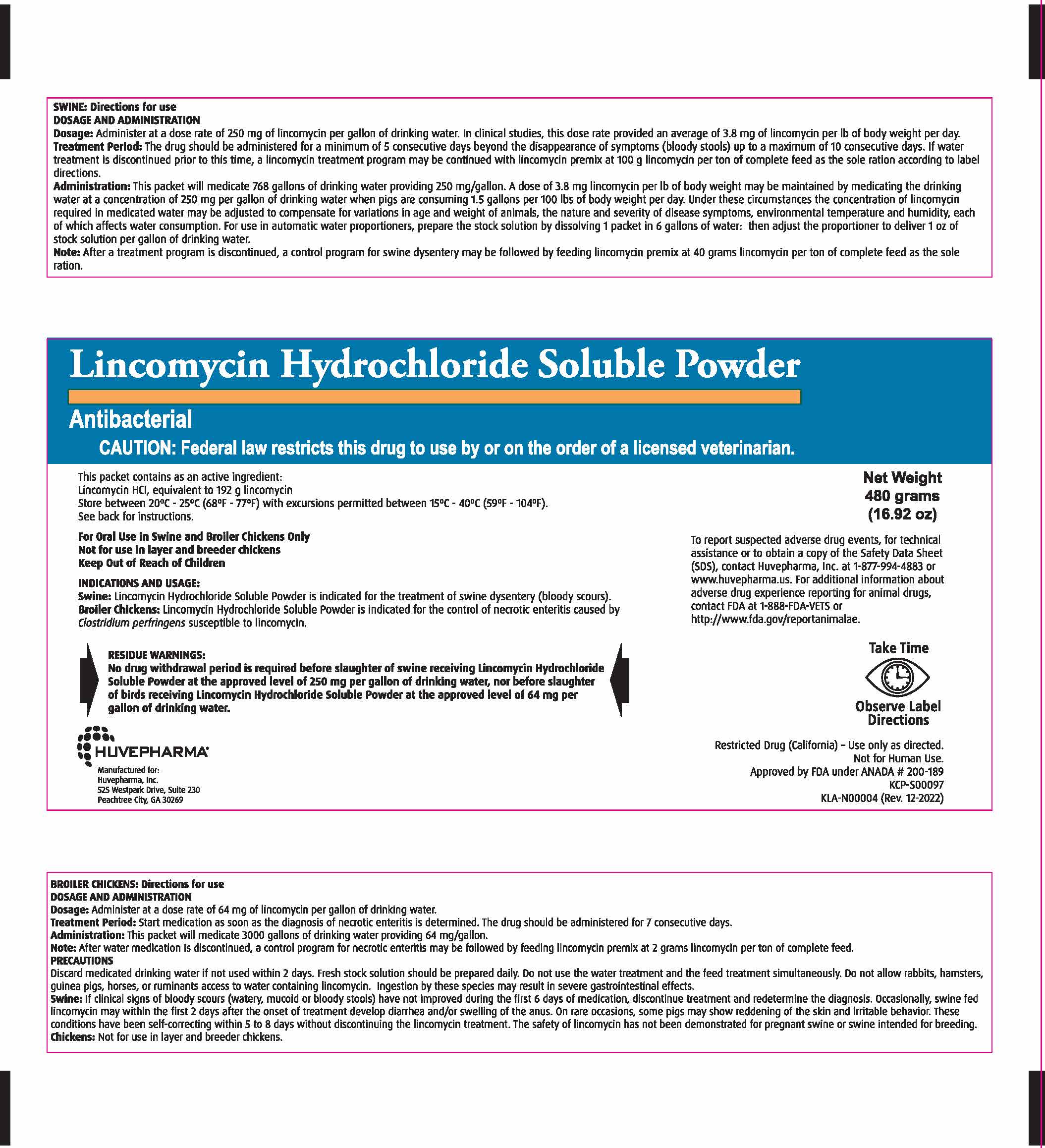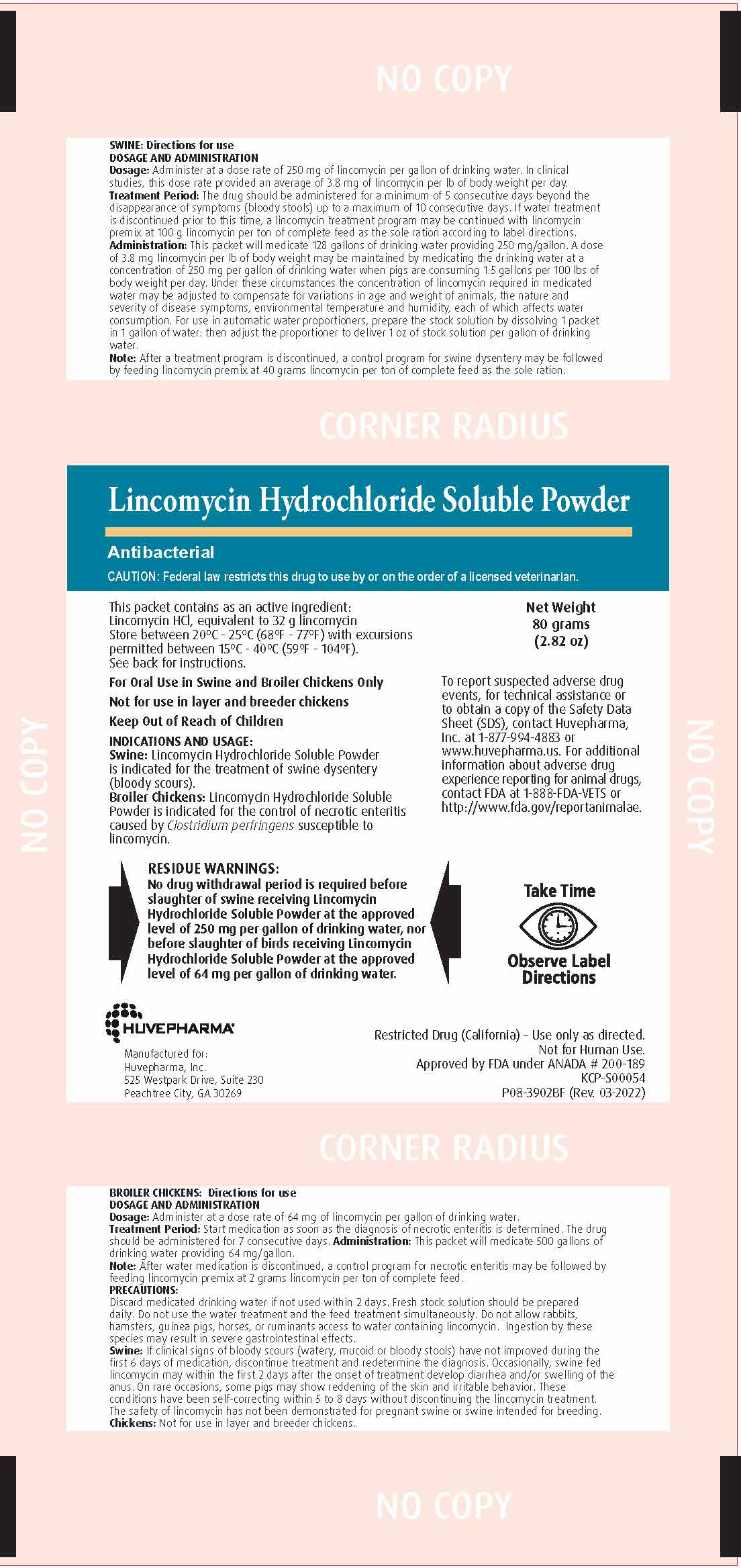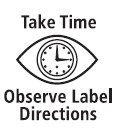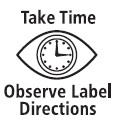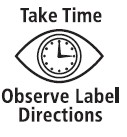 DRUG LABEL: Lincomycin Hydrochloride Soluble Powder
NDC: 23243-6752 | Form: POWDER, FOR SOLUTION
Manufacturer: Huvepharma, Inc.
Category: animal | Type: PRESCRIPTION ANIMAL DRUG LABEL
Date: 20241214

ACTIVE INGREDIENTS: LINCOMYCIN HYDROCHLORIDE 0.4 g/1 g

80 Gram Front Panel

Lincomycin Hydrochloride Soluble Powder
Antibacterial

GENERAL PRECAUTIONS

CAUTION: Federal law restricts this drug to use by or on the order of a licensed veterinarian.

STORAGE AND HANDLING

This packet contains as an active ingredient:
Lincomycin HCl, equivalent to 32 g lincomycin
Store between 20˚C - 25˚C (68˚F - 77˚F) with excursions permitted
between 15˚C - 40˚C (59˚F - 104˚F).
See back for instructions.

Net Weight
80 grams
(2.82 oz)

80 g front panel

For Oral Use in Swine and Broiler Chickens Only
Not for use in layer and breeder chickens
Keep Out of Reach of Children

INDICATIONS AND USAGE:
Swine: Lincomycin Hydrochloride Soluble Powder is indicated for the treatment of swine dysentery (bloody scours).
Broiler Chickens: Lincomycin Hydrochloride Soluble Powder is indicated for the control of necrotic enteritis caused
by Clostridium perfringens susceptible to lincomycin.

ADVERSE REACTIONS

To report suspected adverse drug events, for technical assistance or
to obtain a copy of the Safety Data Sheet (SDS), contact Huvepharma,
Inc. at 1-877-994-4883 or www.huvepharma.us. For additional
information about adverse drug experience reporting for animal drugs,
contact FDA at 1-888-FDA-VETS or http://www.fda.gov/reportanimalae.

RESIDUE WARNINGS:
No drug withdrawal period is required before slaughter of swine receiving Lincomycin Hydrochloride
Soluble Powder at the approved level of 250 mg per gallon of drinking water, nor before slaughter
of birds receiving Lincomycin Hydrochloride Soluble Powder at the approved level of 64 mg per
gallon of drinking water.

Huvepharma®
Manufactured for:
Huvepharma, Inc.
525 Westpark Drive, Suite 230
Peachtree City, GA 30269

Restricted Drug (California) - Use only as directed.
Not for Human Use.
Approved by FDA under ANADA # 200-189
KCP-S00054
P08-3902BF (Rev. 03-2022)

DOSAGE AND ADMINISTRATION

BROILER CHICKENS: Directions for use
DOSAGE AND ADMINISTRATION
Dosage: Administer at a dose rate of 64 mg of lincomycin per gallon of drinking water.
Treatment Period: Start medication as soon as the diagnosis of necrotic enteritis is determined. The drug
should be administered for 7 consecutive days. Administration: This packet will medicate 500 gallons of
drinking water providing 64 mg/gallon.
Note: After water medication is discontinued, a control program for necrotic enteritis may be followed by
feeding lincomycin premix at 2 grams lincomycin per ton of complete feed.

PRECAUTIONS:
Discard medicated drinking water if not used within 2 days. Fresh stock solution should be prepared
daily. Do not use the water treatment and the feed treatment simultaneously. Do not allow rabbits,
hamsters, guinea pigs, horses, or ruminants access to water containing lincomycin. Ingestion by these
species may result in severe gastrointestinal effects.
Swine: If clinical signs of bloody scours (watery, mucoid or bloody stools) have not improved during the
first 6 days of medication, discontinue treatment and redetermine the diagnosis. Occasionally, swine fed
lincomycin may within the first 2 days after the onset of treatment develop diarrhea and/or swelling of the
anus. On rare occasions, some pigs may show reddening of the skin and irritable behavior. These
conditions have been self-correcting within 5 to 8 days without discontinuing the lincomycin treatment.
The safety of lincomycin has not been demonstrated for pregnant swine or swine intended for breeding.
Chickens: Not for use in layer and breeder chickens.

DOSAGE AND ADMINISTRATION

SWINE: Directions for use
DOSAGE AND ADMINISTRATION
Dosage: Administer at a dose rate of 250 mg of lincomycin per gallon of drinking water. In clinical
studies, this dose rate provided an average of 3.8 mg of lincomycin per lb of body weight per day.
Treatment Period: The drug should be administered for a minimum of 5 consecutive days beyond the
disappearance of symptoms (bloody stools) up to a maximum of 10 consecutive days. If water treatment
is discontinued prior to this time, a lincomycin treatment program may be continued with lincomycin
premix at 100 g lincomycin per ton of complete feed as the sole ration according to label directions.
Administration: This packet will medicate 128 gallons of drinking water providing 250 mg/gallon. A dose
of 3.8 mg lincomycin per lb of body weight may be maintained by medicating the drinking water at a
concentration of 250 mg per gallon of drinking water when pigs are consuming 1.5 gallons per 100 lbs of
body weight per day. Under these circumstances the concentration of lincomycin required in medicated
water may be adjusted to compensate for variations in age and weight of animals, the nature and
severity of disease symptoms, environmental temperature and humidity, each of which affects water
consumption. For use in automatic water proportioners, prepare the stock solution by dissolving 1 packet
in 1 gallon of water: then adjust the proportioner to deliver 1 oz of stock solution per gallon of drinking
water.
Note: After a treatment program is discontinued, a control program for swine dysentery may be followed
by feeding lincomycin premix at 40 grams lincomycin per ton of complete feed as the sole ration.

160 Gram Front Panel

Lincomycin Hydrochloride Soluble Powder
Antibacterial

GENERAL PRECAUTIONS

CAUTION: Federal law restricts this drug to use by or on the order of a licensed veterinarian.

STORAGE AND HANDLING

This packet contains as an active ingredient:
Lincomycin HCl, equivalent to 64 g lincomycin

Store between 20˚C - 25˚C (68˚F - 77˚F) with excursions permitted
between 15˚C - 40˚C (59˚F - 104˚F). See back for instructions.

Net Weight
160 grams
(5.64 oz)

INDICATIONS AND USAGE

For Oral Use in Swine and Broiler Chickens Only

Not for use in layer or breeder chickens

Keep Out of Reach of Children

INDICATIONS AND USAGE:

Swine: Lincomycin Hydrochloride Soluble Powder is indicated for the treatment of swine dysentery (bloody scours).

Broiler Chickens: Lincomycin Hydrochloride Soluble Powder is indicated for the control of necrotic enteritis caused
by Clostridium perfringens susceptible to lincomycin.

ADVERSE REACTIONS

To report suspected adverse drug events, for technical assistance or
to obtain a copy of the Safety Data Sheet (SDS), contact Huvepharma,
Inc. at 1-877-994-4883 or www.huvepharma.us. For additional
information about adverse drug experience reporting for animal drugs,
contact FDA at 1-888-FDA-VETS or http://www.fda.gov/reportanimalae.

RESIDUE WARNINGS:
No drug withdrawal period is required before slaughter of swine receiving Lincomycin Hydrochloride
Soluble Powder at the approved level of 250 mg per gallon of drinking water, nor before slaughter
of birds receiving Lincomycin Hydrochloride Soluble Powder at the approved level of 64 mg per
gallon of drinking water.

Huvepharma®
Manufactured for:
Huvepharma, Inc.
525 Westpark Drive, Suite 230
Peachtree City, GA 30269

Restricted Drug (California) - Use only as directed.
Not for Human Use.
Approved by FDA under ANADA # 200-189
KCP-S00093
P08-3903BF (Rev. 03-2022)

DOSAGE AND ADMINISTRATION

BROILER CHICKENS: Directions for use
DOSAGE AND ADMINISTRATION
Dosage: Administer at a dose rate of 64 mg of lincomycin per gallon of drinking water.
Treatment Period: Start medication as soon as the diagnosis of necrotic enteritis is determined. The drug should be administered for 7
consecutive days.
Administration: This packet will medicate 1000 gallons of drinking water providing 64 mg/gallon.
Note: After water medication is discontinued, a control program for necrotic enteritis may be followed by feeding lincomycin premix at 2
grams lincomycin per ton of complete feed.

PRECAUTIONS:
Discard medicated drinking water if not used within 2 days. Fresh stock solution should be prepared daily. Do not use the water
treatment and the feed treatment simultaneously. Do not allow rabbits, hamsters, guinea pigs, horses, or ruminants access to water
containing lincomycin. Ingestion by these species may result in severe gastrointestinal effects.
Swine: If clinical signs of bloody scours (watery, mucoid or bloody stools) have not improved during the first 6 days of medication,
discontinue treatment and redetermine the diagnosis. Occasionally, swine fed lincomycin may within the first 2 days after the onset of
treatment develop diarrhea and/or swelling of the anus. On rare occasions, some pigs may show reddening of the skin and irritable
behavior. These conditions have been self-correcting within 5 to 8 days without discontinuing the lincomycin treatment. The safety of
lincomycin has not been demonstrated for pregnant swine or swine intended for breeding.
Chickens: Not for use in layer and breeder chickens.

DOSAGE AND ADMINISTRATION

SWINE: Directions for use
DOSAGE AND ADMINISTRATION
Dosage: Administer at a dose rate of 250 mg of lincomycin per gallon of drinking water. In clinical studies, this dose rate provided an
average of 3.8 mg of lincomycin per lb of body weight per day.
Treatment Period: The drug should be administered for a minimum of 5 consecutive days beyond the disappearance of symptoms
(bloody stools) up to a maximum of 10 consecutive days. If water treatment is discontinued prior to this time, a lincomycin
treatment program may be continued with lincomycin premix at 100 g lincomycin per ton of complete feed as the sole ration
according to label directions.
Administration: This packet will medicate 256 gallons of drinking water providing 250 mg/gallon. A dose of 3.8 mg lincomycin per lb
of body weight may be maintained by medicating the drinking water at a concentration of 250 mg per gallon of drinking water when
pigs are consuming 1.5 gallons per 100 lbs of body weight per day. Under these circumstances the concentration of lincomycin
required in medicated water may be adjusted to compensate for variations in age and weight of animals, the nature and severity of
disease symptoms, environmental temperature and humidity, each of which affects water consumption. For use in automatic water
proportioners, prepare the stock solution by dissolving 1 packet in 2 gallons of water: then adjust the proportioner to deliver 1 oz of
stock solution per gallon of drinking water.
Note: After a treatment program is discontinued, a control program for swine dysentery may be followed by feeding lincomycin
premix at 40 grams lincomycin per ton of complete feed as the sole ration.

480 Gram Front Panel

Lincomycin Hydrochloride Soluble Powder
Antibacterial

PRECAUTIONS

CAUTION: Federal law restricts this drug to use by or on the order of a licensed veterinarian.

STORAGE AND HANDLING

This packet contains as an active ingredient:
Lincomycin HCl, equivalent to 192 g lincomycin
Store between 20˚C - 25˚C (68˚F - 77˚F) with excursions permitted between 15˚C - 40˚C (59˚F - 104˚F).
See back for instructions.

Net Weight
480 grams
(16.92 oz)

VETERINARY INDICATIONS

For Oral Use in Swine and Broiler Chickens Only
Not for use in layer and breeder chickens
Keep Out of Reach of Children

INDICATIONS AND USAGE:

Swine: Lincomycin Hydrochloride Soluble Powder is indicated
for the treatment of swine dysentery (bloody scours).
Broiler Chickens: Lincomycin Hydrochloride Soluble Powder is
indicated for the control of necrotic enteritis caused by Clostridium
perfringens susceptible to lincomycin.

ADVERSE REACTIONS

To report suspected adverse drug events, for technical assistance or
to obtain a copy of the Safety Data Sheet (SDS), contact Huvepharma,
Inc. at 1-877-994-4883 or www.huvepharma.us. For additional
information about adverse drug experience reporting for animal drugs,
contact FDA at 1-888-FDA-VETS or http://www.fda.gov/reportanimalae.

RESIDUE WARNINGS:
No drug withdrawal period is required before slaughter of
swine receiving Lincomycin Hydrochloride Soluble Powder at
the approved level of 250 mg per gallon of drinking water, nor
before slaughter of birds receiving Lincomycin Hydrochloride
Soluble Powder at the approved level of 64 mg per gallon of
drinking water.

Huvepharma®
Manufactured for:
Huvepharma, Inc.
525 Westpark Drive, Suite 230
Peachtree City, GA 30269

Restricted Drug (California) - Use only as directed.
Not for Human Use.
Approved by FDA under ANADA # 200-189
KCP-S00097
KLA-N00004 (Rev. 12-2022)

DOSAGE AND ADMINISTRATION

BROILER CHICKENS: Directions for use
DOSAGE AND ADMINISTRATION
Dosage: Administer at a dose rate of 64 mg of lincomycin per gallon of drinking water.
Treatment Period: Start medication as soon as the diagnosis of necrotic enteritis is determined. The drug should be administered for 7
consecutive days.
Administration: This packet will medicate 3000 gallons of drinking water providing 64 mg/gallon.
Note: After water medication is discontinued, a control program for necrotic enteritis may be followed by feeding lincomycin premix at 2
grams lincomycin per ton of complete feed.

PRECAUTIONS:
Discard medicated drinking water if not used within 2 days. Fresh stock solution
should be prepared daily. Do not use the water treatment and the feed treatment
simultaneously. Do not allow rabbits, hamsters, guinea pigs, horses, or ruminants
access to water containing lincomycin. Ingestion by these species may result in
severe gastrointestinal effects.
Swine: If clinical signs of bloody scours (watery, mucoid or bloody stools) have
not improved during the first 6 days of medication, discontinue treatment and
redetermine the diagnosis. Occasionally, swine fed lincomycin may within the
first 2 days after the onset of treatment develop diarrhea and/or swelling of
the anus. On rare occasions, some pigs may show reddening of the skin and irritable
behavior. These conditions have been self-correcting within 5 to 8 days without
discontinuing the lincomycin treatment. The safety of lincomycin has not been
demonstrated for pregnant swine or swine intended for breeding.
Chickens: Not for use in layer and breeder chickens.

DOSAGE AND ADMINISTRATION

SWINE: Directions for use
DOSAGE AND ADMINISTRATION
Dosage: Administer at a dose rate of 250 mg of lincomycin per gallon of drinking water. In clinical studies, this dose rate provided an average of 3.8 mg of lincomycin per lb of body weight per day.
Treatment Period: The drug should be administered for a minimum of 5 consecutive days beyond the disappearance of symptoms (bloody stools) up to a maximum of 10 consecutive days. If water treatment is discontinued prior to this time, a lincomycin treatment program may be continued with lincomycin premix at 100 g lincomycin per ton of complete feed as the sole ration according to label directions.
Administration: This packet will medicate 768 gallons of drinking water providing 250 mg/gallon. A dose of 3.8 mg lincomycin per lb of body weight may be maintained by medicating the drinking water at a concentration of 250 mg per gallon of drinking water when pigs are consuming 1.5 gallons per 100 lbs of body weight per day. Under these circumstances the concentration of lincomycin required in medicated water may be adjusted to compensate for variations in age and weight of animals, the nature and severity of disease symptoms, environmental temperature and humidity, each of which affects water consumption. For use in automatic water proportioners, prepare the stock solution by dissolving 1 packet in 6 gallons of water: then adjust the proportioner to deliver 1 oz of stock solution per gallon of drinking water.
Note: After a treatment program is discontinued, a control program for swine dysentery may be followed by feeding lincomycin premix at 40 grams lincomycin per ton of complete feed as the sole ration.